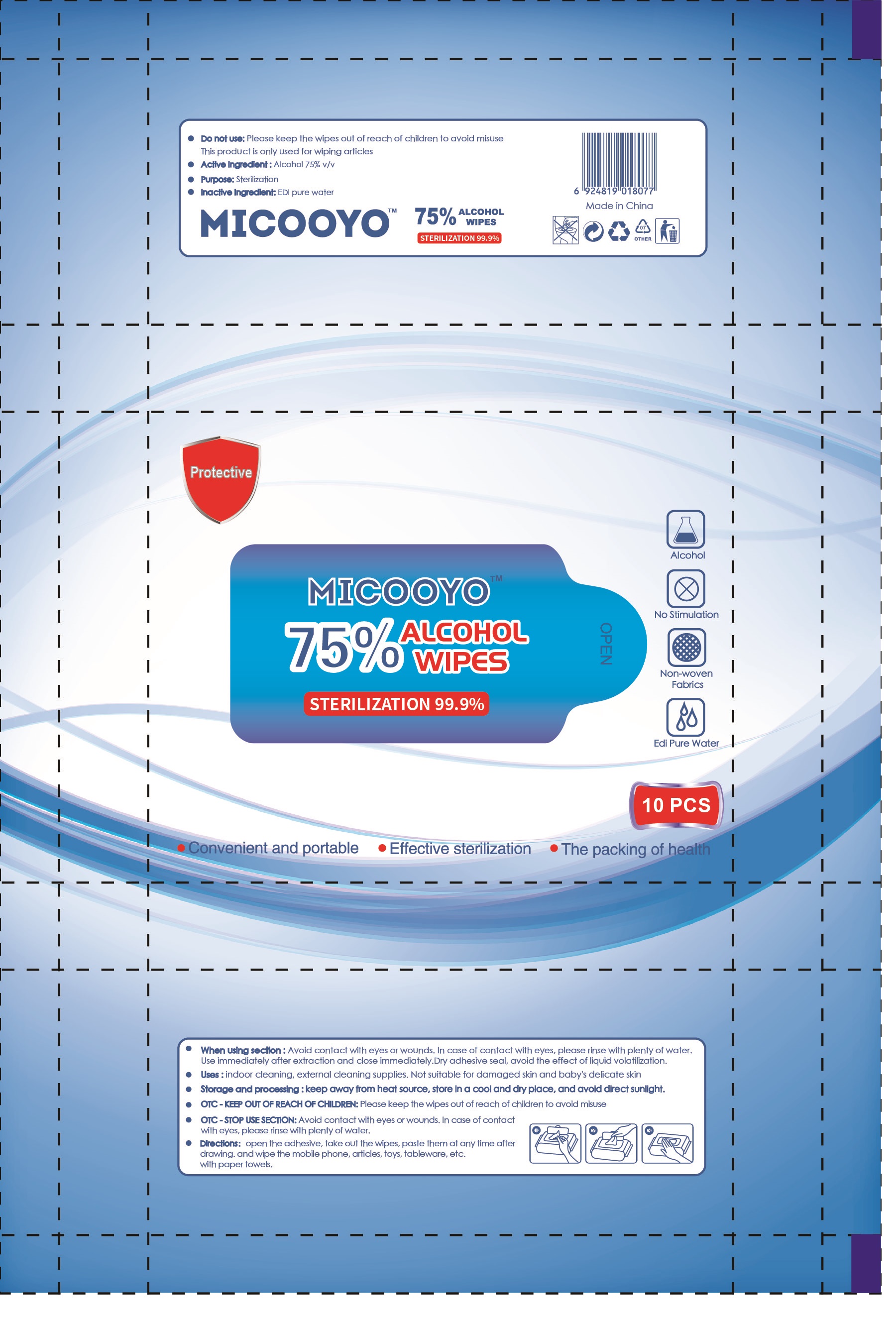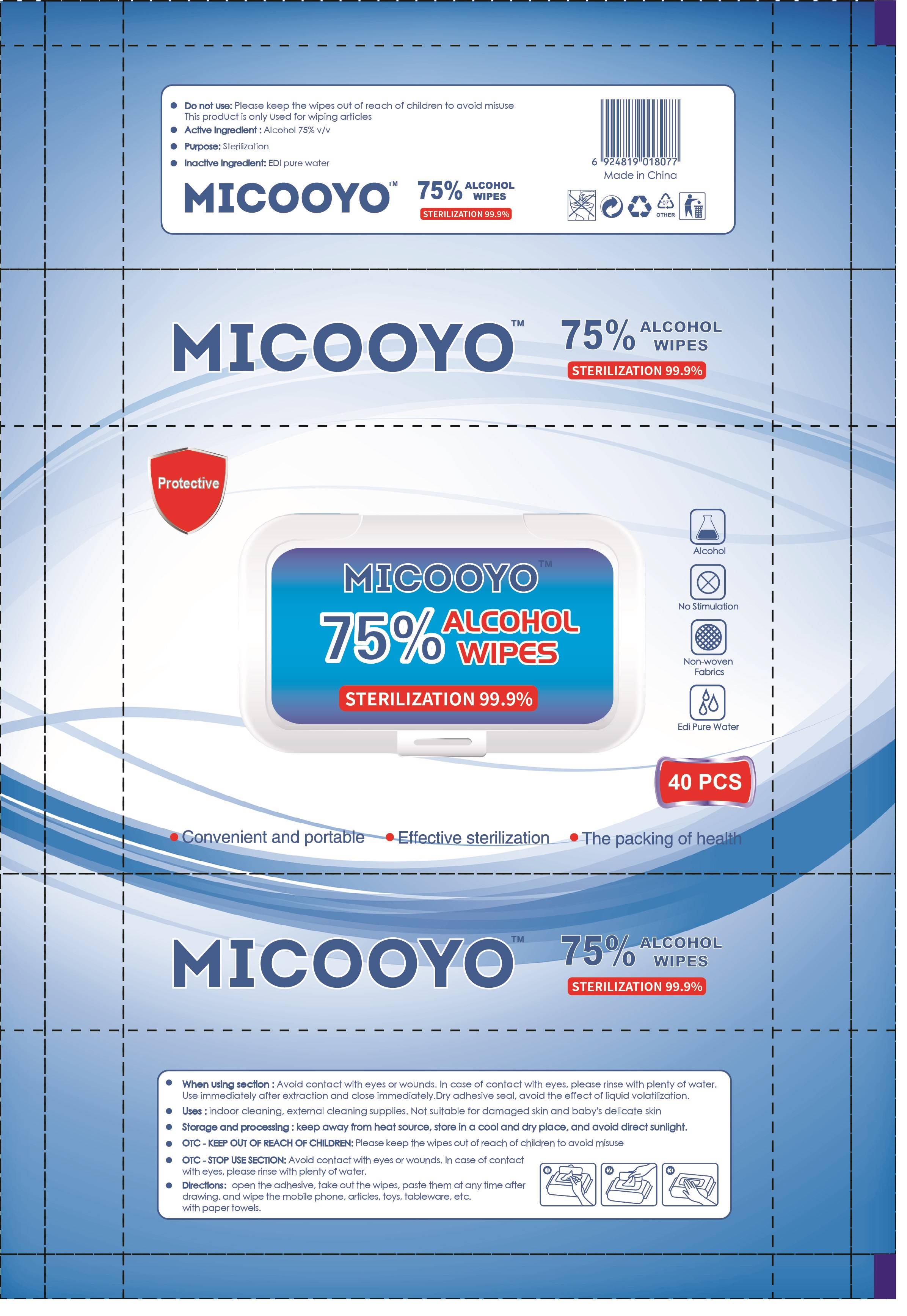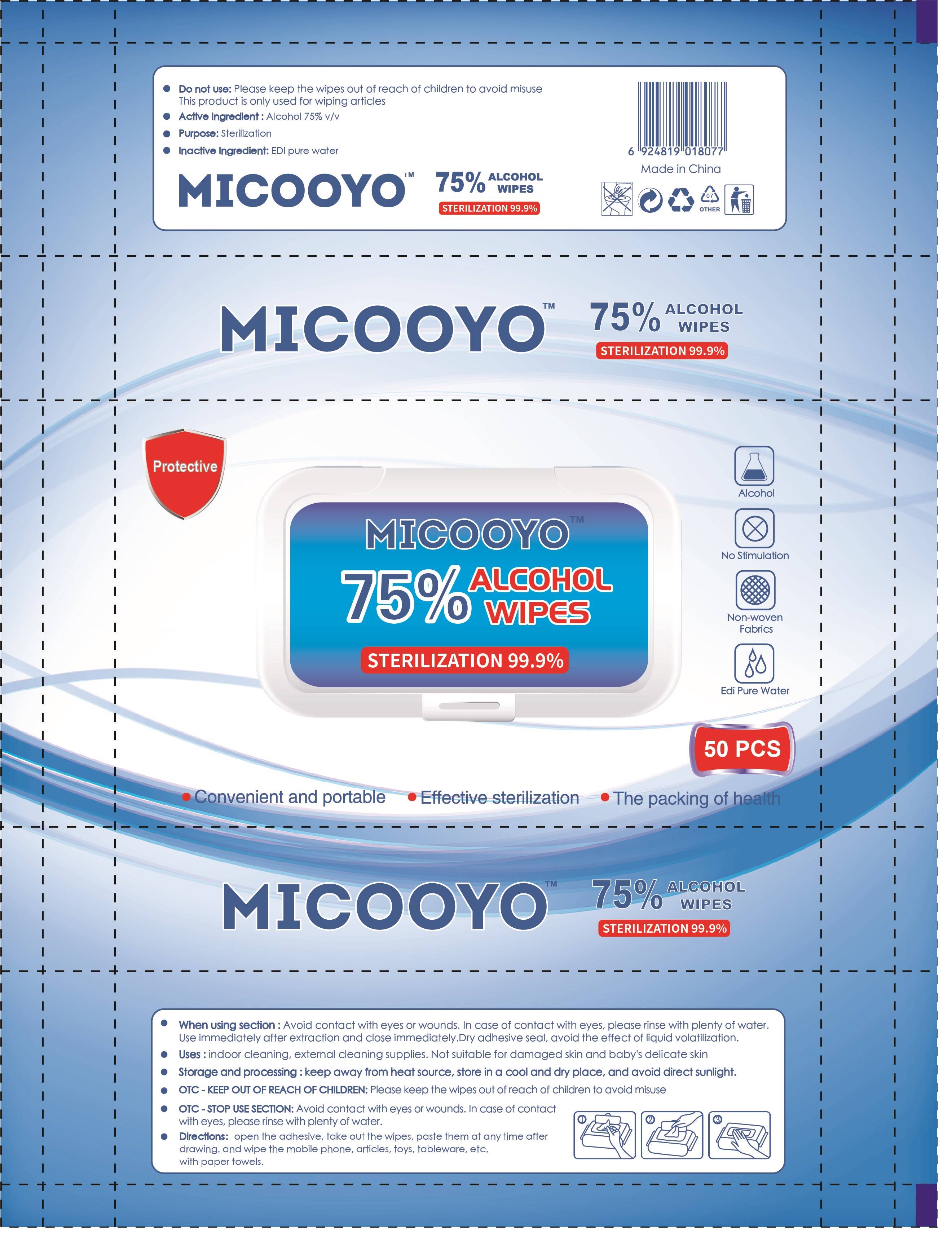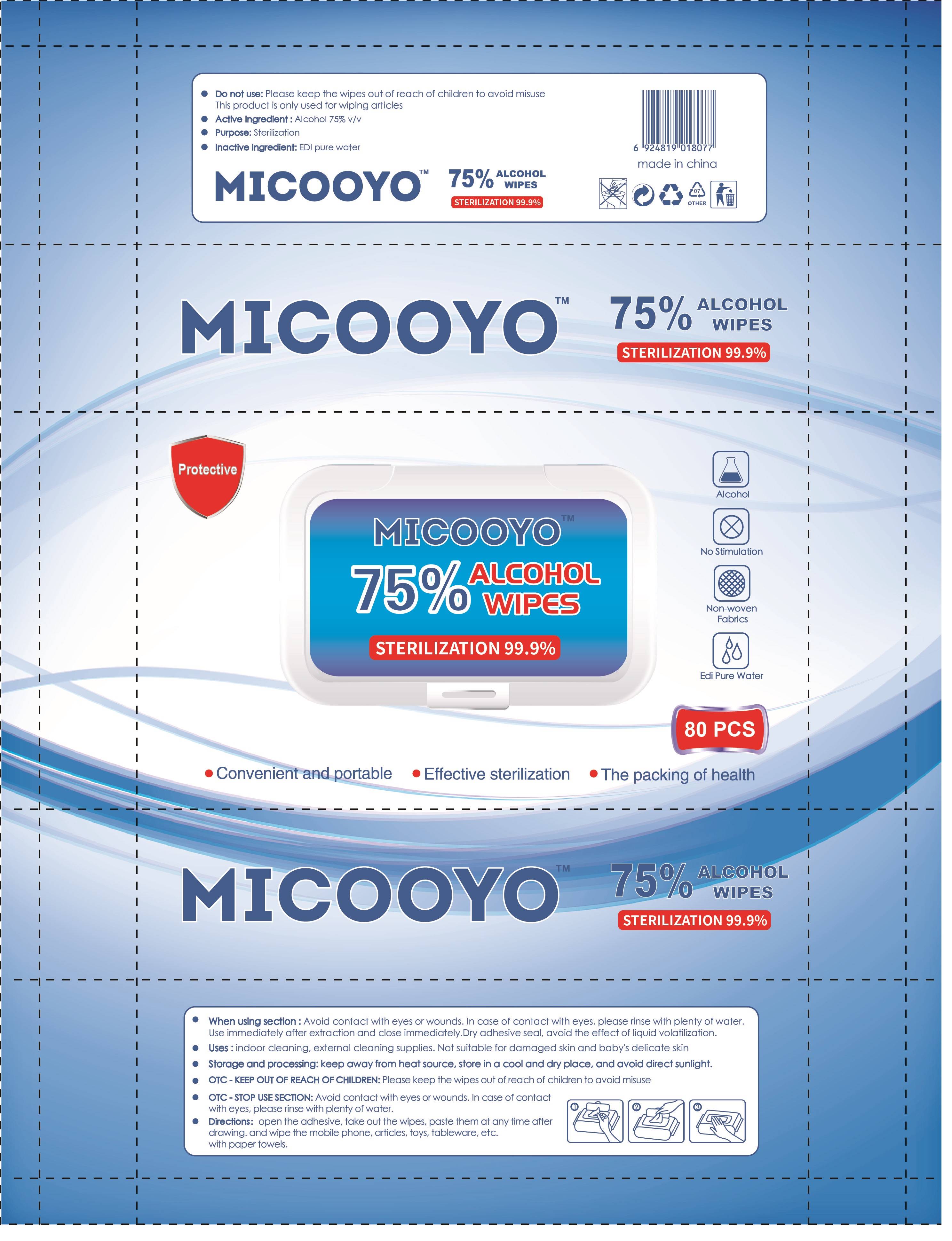 DRUG LABEL: ALCOHOL WIPES
NDC: 79735-001 | Form: CLOTH
Manufacturer: WHARNEY DAILY CHEMICAL CO.,LTD
Category: otc | Type: HUMAN OTC DRUG LABEL
Date: 20200727

ACTIVE INGREDIENTS: ALCOHOL 75 1/100 1
INACTIVE INGREDIENTS: WATER

ALCOHOL WIPES

Purpose

Sterilization

Use

indoor cleaning, external cleaning supplies. Not suitable for damaged skin and baby's delicate skin

Warnings

keep away from heat source, store in a cool and dry place, and avoid direct sunlight.

Do not use

Please keep the wipes out of reach of children to avoid misuse

This product is only used for wiping articles

WHEN USING

Avoid contact with eyes or wounds. In case of contact with eyes, please rinse with plenty of water.

Use immediately after extraction and close immediately.Dry adhesive seal, avoid the effect of liquid volatilization.

STOP USE

Avoid contact with eyes or wounds. In case of contact with eyes, please rinse with plenty of water.

KEEP OUT OF REACH OF CHILDREN

Please keep the wipes out of reach of children to avoid misuse

Directions

open the adhesive, take out the wipes, paste them at any time after drawing. and wipe the mobile phone, articles, toys, tableware, etc. with paper towels.

Other information

/

Inactive ingredients

EDI pure water